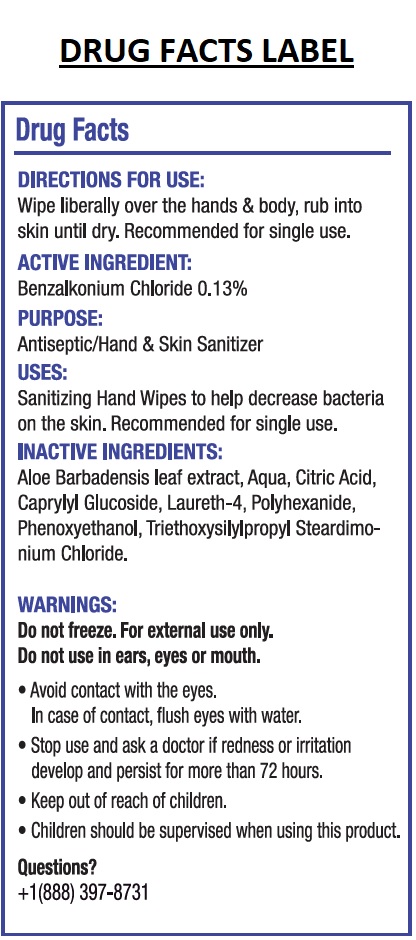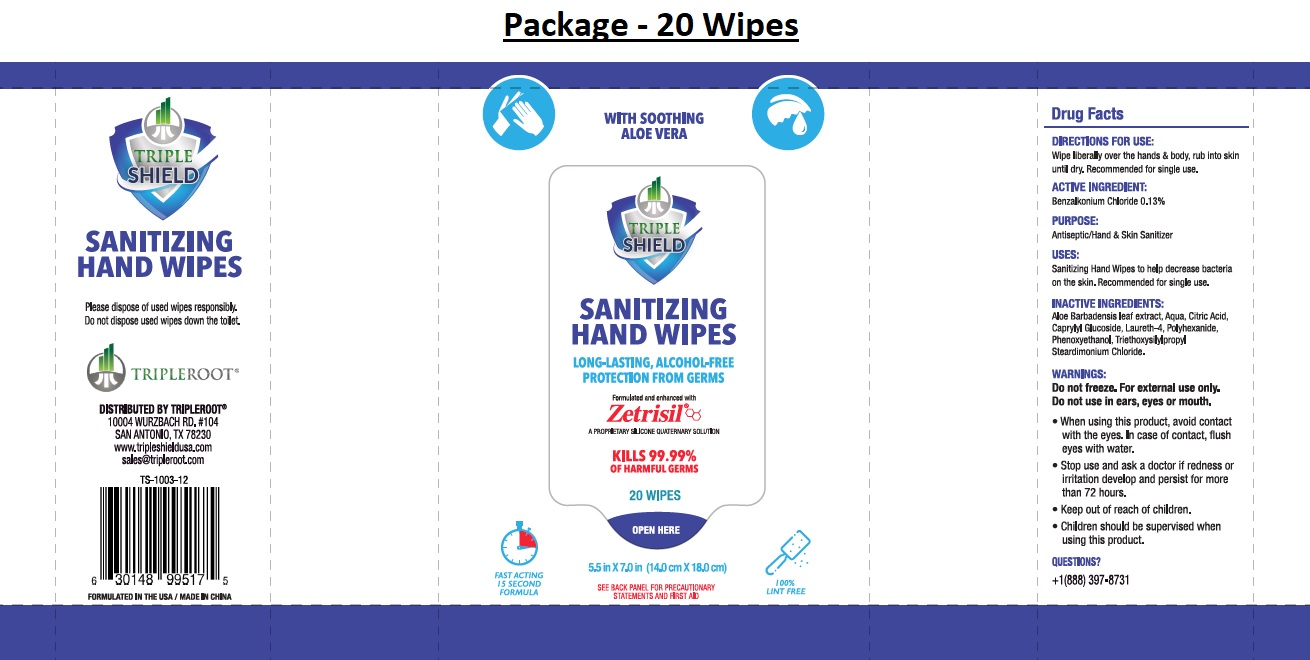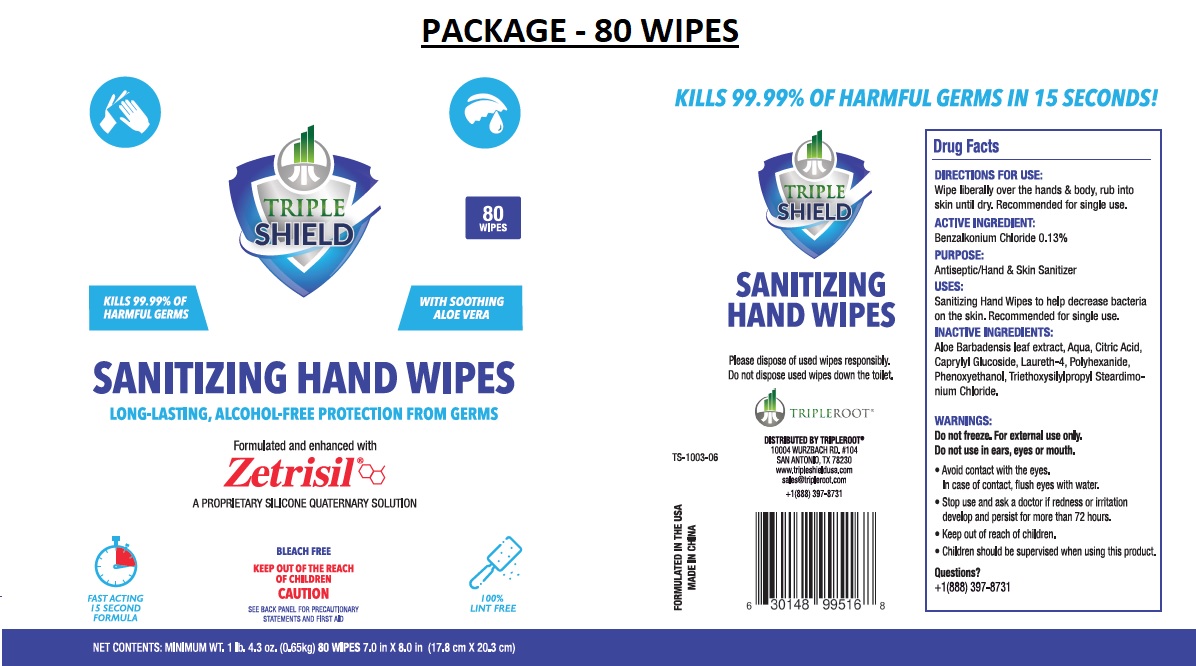 DRUG LABEL: TRIPLE SHIELD SANITIZING HAND WIPES
NDC: 71884-030 | Form: CLOTH
Manufacturer: Enviro Specialty Chemicals Inc
Category: otc | Type: HUMAN OTC DRUG LABEL
Date: 20211209

ACTIVE INGREDIENTS: BENZALKONIUM CHLORIDE 0.13 g/100 mL
INACTIVE INGREDIENTS: ALOE VERA LEAF; WATER; CITRIC ACID MONOHYDRATE; CAPRYLYL GLUCOSIDE; LAURETH-4; POLIHEXANIDE; PHENOXYETHANOL; TRIETHOXYSILYLPROPYL STEARDIMONIUM CHLORIDE

TRIPLE SHIELD SANITIZING HAND WIPES

DIRECTIONS FOR USE:

Wipe liberally over the hands & body, rub into skin until dry. Recommended for single use.

ACTIVE INGREDIENT:

Benzalkonium Chloride 0.13%

PURPOSE:

Antiseptic/Hand & Skin Sanitizer

USES:

Sanitizing Hand Wipes to help decrease bacteria on the skin. Recommended for single use.

INACTIVE INGREDIENTS:

Aloe Barbadensis leaf extract, Aqua, Citric Acid, Caprylyl Glucoside, Laureth-4, Polyhexanide, Phenoxyethanol, Triethoxysilylpropyl steardimonium

Chloride.

WARNINGS:

Do not freeze. For external use only.

Do not use in ears, eyes or mouth.

• When using this product, avoid contact with the eyes. In case of contact, flush eyes with water.

• Stop use and ask a doctor if redness or irritation develop and persist for more than 72 hours.

• Keep out of reach of children.

• Children should be supervised when using this product.

QUESTIONS?

+1(888) 397-8731

WITH SOOTHING ALOE VERA

LONG-LASTING, ALCOHOL-FREE PROTECTION FROM GERMS

Formulated and enhanced with

Zetrisil®

A PROPRIETARY SILICONE QUATERNARY SOLUTION

KILLS 99.99% OF HARMFUL GERMS IN 15 SECONDS!

FAST ACTING 15 SECOND FORMULA

SEE BACK PANEL FOR PRECAUTIONARY STATEMENTS AND FIRST AID

100% LINT FREE

BLEACH FREE

Please dispose of used wipes responsibly.

Do not dispose used wipes down the toilet.

DISTRIBUTED BY TRIPLEROOT®

10004 WURZBACH RD. #104

SAN ANTONIO, TX 78230

www.tripleshieldusa.com

sales@tripleroot.com

FORMULATED IN THE USA | MADE IN CHINA